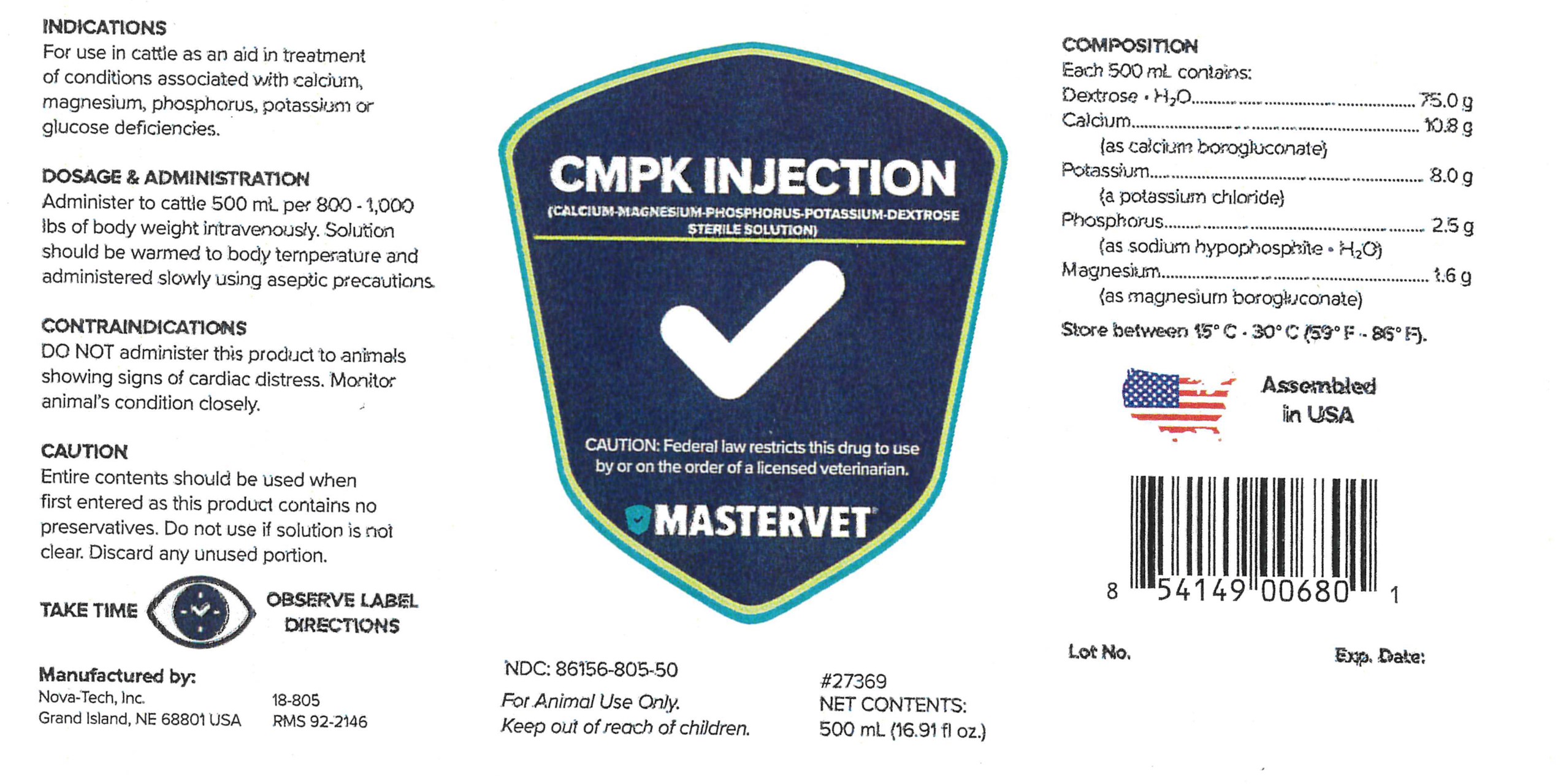 DRUG LABEL: CMPK
NDC: 86156-805 | Form: INJECTION, SOLUTION
Manufacturer: MasterVet
Category: animal | Type: PRESCRIPTION ANIMAL DRUG LABEL
Date: 20230103

ACTIVE INGREDIENTS: Dextrose monohydrate 75.0 g/500 mL; Potassium Chloride 8.0 g/500 mL; Calcium Gluconate Monohydrate 10.8 g/500 mL; Phosphorus 2.5 g/500 mL; Magnesium Gluconate 1.6 g/500 mL

CMPK Injection

Composition

Each 500 mL contains:

Dextrose • H2O.................................... 75.0 g

Calcium .............................................. 10.8 g

(as calcium borogluconate)

Potassium ........................................... 8.0 g

(as potassium chloride)

Phosphorus .......................................... 2.5 g

(as sodium hypophosphite • H2O)

Magnesium ........................................... 1.6 g

(as magnesium borogluconate)

INDICATIONS

For use in cattle as an aid in treatment of conditions associated with calcium,
magnesium, phosphorus, potassium or glucose deficiencies.

CONTRAINDICATIONS

DO NOT administer this product to animals showing signs of cardiac distress. Monitor animal's condition closely.

CAUTION

Entire contents should be used when first entered as this product contains no preservatives. Do not use if solution is not clear.
Discard any unused portion.

DOSAGE & ADMINISTRATION:

Administer to cattle 500 mL per 800 - 1,000 lbs of body weight intravenously. Solution should be warmed to body temperature and administered slowly using aseptic precautions.

STORAGE AND HANDLING

Store between 15°C - 30°C (59°F - 86°F).

WARNINGS AND PRECAUTIONS

TAKE TIME OBSERVE LABEL DIRECTIONS

Keep Out of Reach of Children.

VETERINARY INDICATIONS

For Animal Use Only.

INFORMATION FOR OWNERS/CAREGIVERS

Manufactured by:

Nova-Tech, Inc.

Grand Island, NE 68801 USA

18-805

RMS 92-2146

NDC: 86156-805-50

Calcium-Magnesium-Phosphorus-Potassium-Dextrose

Sterile Solution

#27369

Net Contents:

500 mL (16.91 fl oz)

Assembled in USA

Lot No.

Exp. Date:

Caution:

Federal law restricts this drug to use by or on the order of a licensed veterinarian.